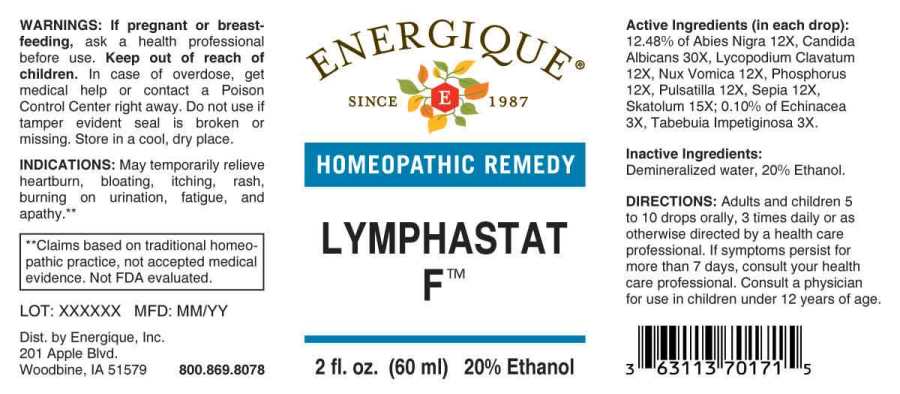 DRUG LABEL: Lymphastat F
NDC: 44911-0604 | Form: LIQUID
Manufacturer: Energique, Inc.
Category: homeopathic | Type: HUMAN OTC DRUG LABEL
Date: 20240305

ACTIVE INGREDIENTS: ECHINACEA ANGUSTIFOLIA WHOLE 3 [hp_X]/1 mL; TABEBUIA IMPETIGINOSA BARK 3 [hp_X]/1 mL; PICEA MARIANA RESIN 12 [hp_X]/1 mL; LYCOPODIUM CLAVATUM SPORE 12 [hp_X]/1 mL; STRYCHNOS NUX-VOMICA SEED 12 [hp_X]/1 mL; PHOSPHORUS 12 [hp_X]/1 mL; PULSATILLA PRATENSIS WHOLE 12 [hp_X]/1 mL; SEPIA OFFICINALIS JUICE 12 [hp_X]/1 mL; SKATOLE 15 [hp_X]/1 mL; CANDIDA ALBICANS 30 [hp_X]/1 mL
INACTIVE INGREDIENTS: WATER; ALCOHOL

Drug Facts:

ACTIVE INGREDIENTS:

(in each drop): 12.48% of Abies Nigra 12X, Candida Albicans 30X, Lycopodium Clavatum 12X, Nux Vomica 12X, Phosphorus 12X, Pulsatilla (Pratensis) 12X, Sepia 12X, Skatolum 15X; 0.10% of Echinacea (Angustifolia) 3X, Tabebuia Impetiginosa 3X.

INDICATIONS:

May temporarily relieve heartburn, bloating, itching, rash, burning on urination, fatigue, and apathy.**

**Claims based on traditional homeopathic practice, not accepted medical evidence. Not FDA evaluated.

WARNINGS:

If pregnant or breast-feeding, ask a health professional before use.

Keep out of reach of children. In case of overdose, get medical help or contact a Poison Control Center right away.

Do not use if tamper evident seal is broken or missing.

Store in a cool, dry place.

Keep out of reach of children. In case of overdose, get medical help or contact a Poison Control Center right away.

DIRECTIONS:

Adults and children 5 to 10 drops orally, 3 times daily or as otherwise directed by a health care professional. If symptoms persist for more than 7 days, consult your health care professional. Consult a physician for use in children under 12 years of age.

INDICATIONS:

May temporarily relieve heartburn, bloating, itching, rash, burning on urination, fatigue, and apathy.**

**Claims based on traditional homeopathic practice, not accepted medical evidence. Not FDA evaluated.

INACTIVE INGREDIENTS:

Demineralized water, 20% Ethanol.

QUESTIONS:

Dist. by Energique, Inc.

201 Apple Blvd.

Woodbine, IA 51579 800.869.8078

PACKAGE LABEL DISPLAY:

ENERGIQUE

SINCE 1987

HOMEOPATHIC REMEDY

LYMPHASTAT

F™

2 fl. oz. (60 ml)